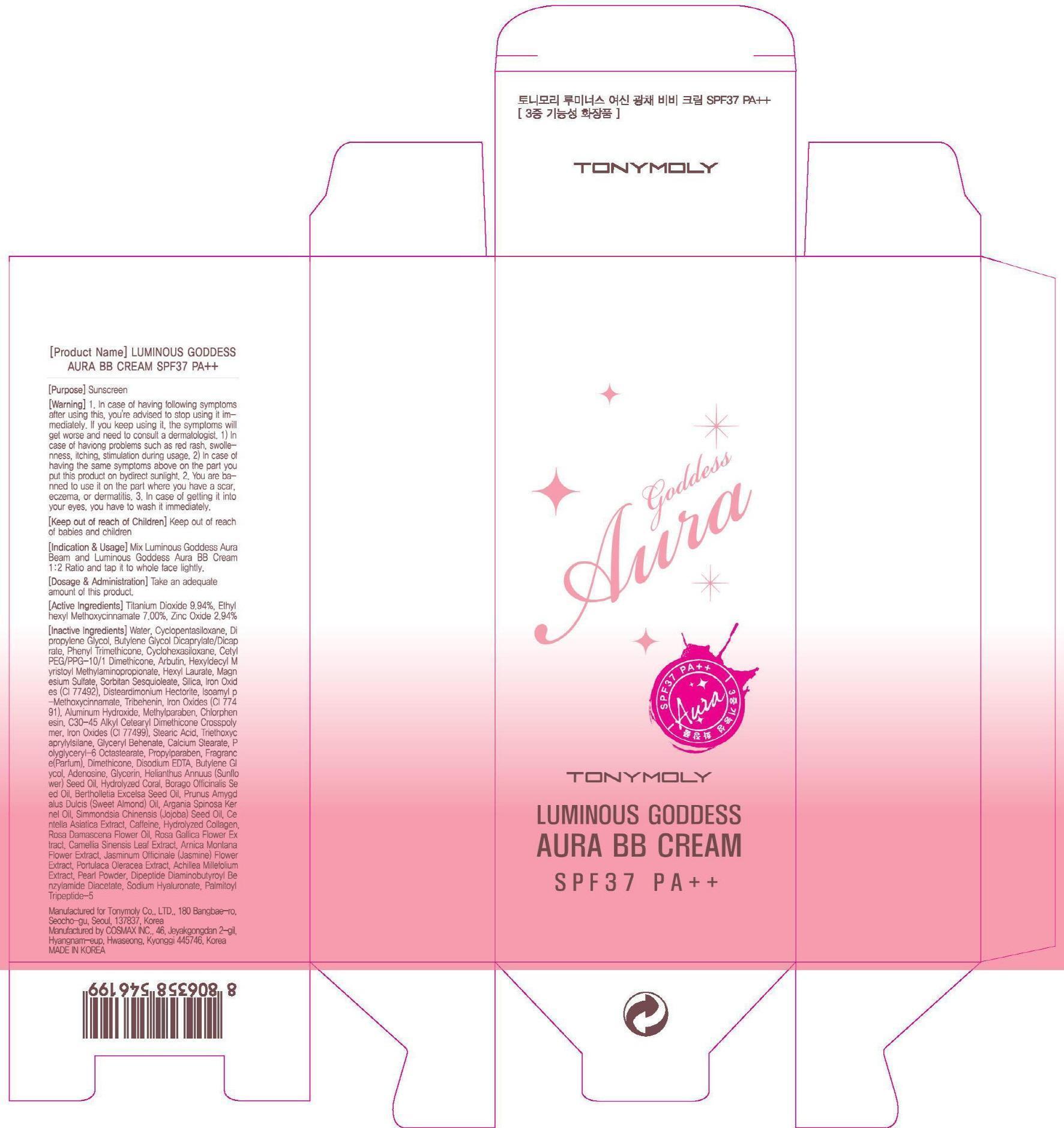 DRUG LABEL: LUMINOUS GODDESS AURA BB
NDC: 59078-042 | Form: CREAM
Manufacturer: TONYMOLY CO., LTD.
Category: otc | Type: HUMAN OTC DRUG LABEL
Date: 20150227

ACTIVE INGREDIENTS: Titanium Dioxide 4.47 g/45 g; OCTINOXATE 3.15 g/45 g; Zinc Oxide 1.32 g/45 g
INACTIVE INGREDIENTS: Water; Dipropylene Glycol

ACTIVE INGREDIENT

Active Ingredients: Titanium Dioxide 9.94%, Ethylhexyl Methoxycinnamate 7.00%, Zinc Oxide 2.94%

INACTIVE INGREDIENT

Inactive Ingredients: Water, Cyclopentasiloxane, Dipropylene Glycol, Butylene Glycol Dicaprylate/Dicaprate, Phenyl Trimethicone, Cyclohexasiloxane, Cetyl PEG/PPG-10/1 Dimethicone, Arbutin, Hexyldecyl Myristoyl Methylaminopropionate, Hexyl Laurate, Magnesium Sulfate, Sorbitan Sesquioleate, Silica, Iron Oxides (CI 77492), Disteardimonium Hectorite, Isoamyl p-Methoxycinnamate, Tribehenin, Iron Oxides (CI 77491), Aluminum Hydroxide, Methylparaben, Chlorphenesin, C30-45 Alkyl Cetearyl Dimethicone Crosspolymer, Iron Oxides (CI 77499), Stearic Acid, Triethoxycaprylylsilane, Glyceryl Behenate, Calcium Stearate, Polyglyceryl-6 Octastearate, Propylparaben, Fragrance(Parfum), Dimethicone, Disodium EDTA, Butylene Glycol, Adenosine, Glycerin, Helianthus Annuus (Sunflower) Seed Oil, Hydrolyzed Coral, Borago Officinalis Seed Oil, Bertholletia Excelsa Seed Oil, Prunus Amygdalus Dulcis (Sweet Almond) Oil, Argania Spinosa Kernel Oil, Simmondsia Chinensis (Jojoba) Seed Oil, Centella Asiatica Extract, Caffeine, Hydrolyzed Collagen, Rosa Damascena Flower Oil, Rosa Gallica Flower Extract, Camellia Sinensis Leaf Extract, Arnica Montana Flower Extract, Jasminum Officinale (Jasmine) Flower Extract, Portulaca Oleracea Extract, Achillea Millefolium Extract, Pearl Powder, Dipeptide Diaminobutyroyl Benzylamide Diacetate, Sodium Hyaluronate, Palmitoyl Tripeptide-5

PURPOSE

PURPOSE: Sunscreen

WARNINGS

Warnings: 1. In case of having following symptoms after using this, you're advised to stop using it immediately. If you keep using it, the symptoms will get worse and need to consult a dermatologist. 1) In case of having problems such as red rash, swollenness, itching, stimulation during usage. 2) In case of having the same symptoms above on the part you put this product on by direct sunlight. 2. You are banned to use it on the part where you have a scar, eczema, or dermatitis. 3. In case of getting it into your eyes, you have to wash it immediately.

KEEP OUT OF REACH OF CHILDREN

Keep out of reach of babies and children

INDICATIONS & USAGE

INDICATIONS AND USAGE: Mix Luminous Goddess Aura Beam and Luminous Goddess Aura BB Cream 1:2 Ratio and tap it to whole face lightly.

DOSAGE & ADMINISTRATION

DOSAGE AND ADMINISTRATION: Take an adequate amount of this product.

PACKAGE LABEL.PRINCIPAL DISPLAY PANEL

Image of carton